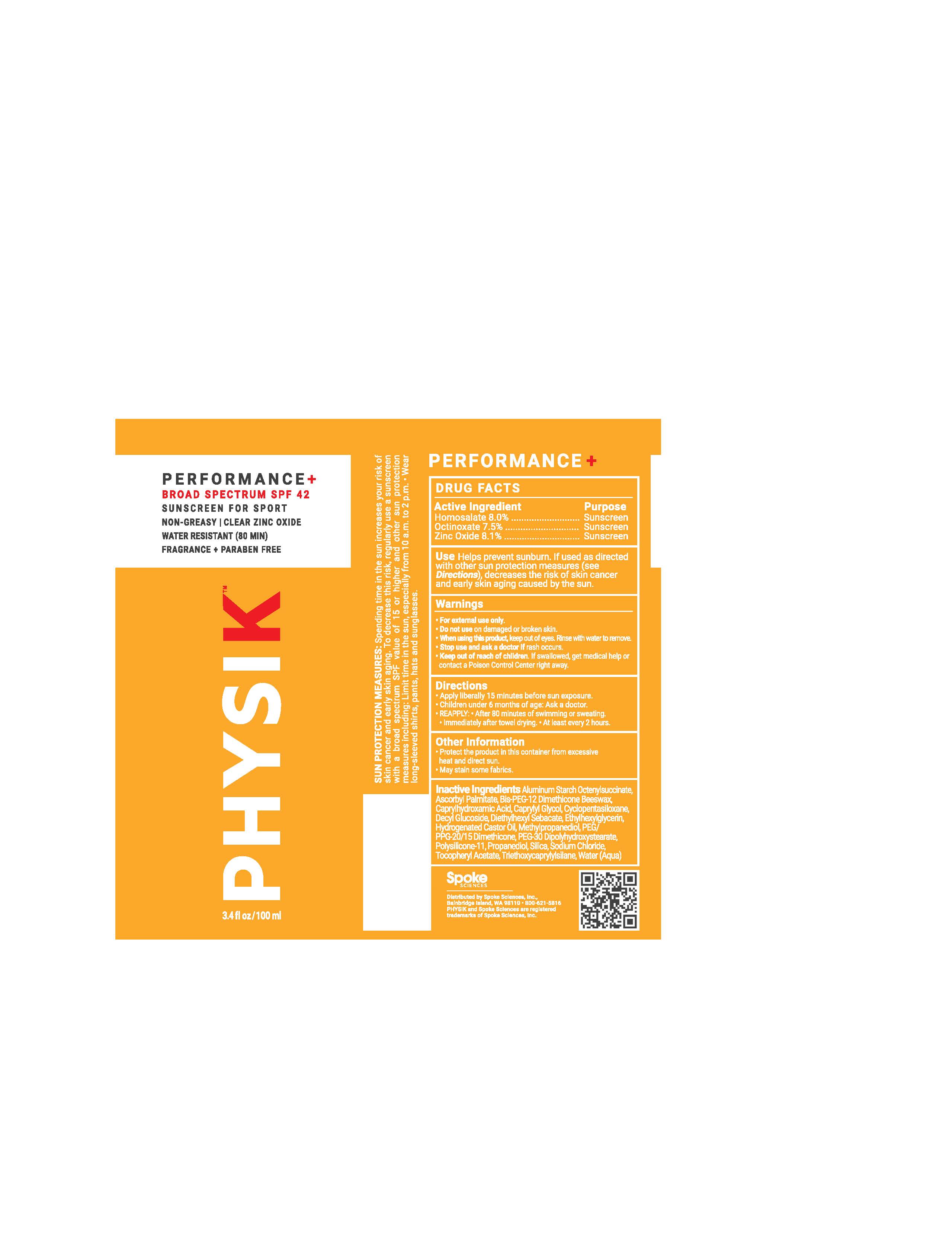 DRUG LABEL: Physik
NDC: 85316-100 | Form: LOTION
Manufacturer: Spoke Sciences, Inc.
Category: otc | Type: HUMAN OTC DRUG LABEL
Date: 20250305

ACTIVE INGREDIENTS: ZINC OXIDE 8.1 g/100 mL; OCTINOXATE 7.5 g/100 mL; HOMOSALATE 8 g/100 mL
INACTIVE INGREDIENTS: BIS-PEG-12 DIMETHICONE (70 MPA.S); ASCORBYL PALMITATE; CYCLOPENTASILOXANE; DIETHYLHEXYL SEBACATE; PEG-30 DIPOLYHYDROXYSTEARATE; ETHYLHEXYLGLYCERIN; CAPRYLHYDROXAMIC ACID; SILICON DIOXIDE; DIMETHICONE/VINYL DIMETHICONE CROSSPOLYMER (SOFT PARTICLE); TRIETHOXYCAPRYLYLSILANE; CAPRYLYL GLYCOL; .ALPHA.-TOCOPHEROL ACETATE; PROPANEDIOL; DECYL GLUCOSIDE; PEG/PPG-20/15 DIMETHICONE; METHYLPROPANEDIOL; HYDROGENATED CASTOR OIL; ALUMINUM STARCH OCTENYLSUCCINATE; SODIUM CHLORIDE; WATER; ETHYLHEXYL PALMITATE

Active Ingredients

Homosalate 8.0%
Octinoxate 7.5%
Zinc Oxide 8.1 %

Purpose

Sunscreen

Uses

Helps prevent sunburn. If used as directed with other sun protection measures (see Directions),decreases the risk of skin cancer and early skin aging caused by the sun.

WARNINGS:

• For external use only.
• Do not use on damaged or broken skin.
• When using this product, keep out of eyes. Rinse with water to remove.
• Stop use and ask a doctor if rash occurs.

- Keep out of reach of children.

If swallowed, get medical help or contact a Poison Control Center right away.

Directions:

• Apply liberally 15 minutes before sun exposure.
• Children under 6 months of age: Ask a doctor.

REAPPLY:

- After 80 minutes of swimming or sweating.
- Immediately after towel drying.
- At least every 2 hours.

Sun Protection Measures. Spending time in the sun increases your risk of skin cancer and early skin aging. To decrease this risk, regularly use a sunscreen with a broad spectrum SPF of 15 or higher and other sun protection measures including:

- Limit time in the sun, especially from 10 a.m. – 2 p.m.

- Wear long sleeves shirts, pants, hats, and sunglasses.

Other Information:

- Protect the product in this container from excessive heat and direct sun.
- May stain some fabrics.

INACTIVE INGREDIENT

ALUMINUM STARCH OCTENYLSUCCINATE,ASCORBYL PALMITATE,BIS-PEG-12 DIMETHICONE (70 MPA.S) (BEESWAX),CAPRYLHYDROXAMIC ACID,CAPRYLYL GLYCOL,CYCLOPENTASILOXANE,DECYL GLUCOSIDE,DIETHYLHEXYL SEBACATE,ETHYLHEXYL METHOXYCINNAMATE,ETHYLHEXYL PALMITATE,ETHYLHEXYLGLYCERIN,HYDROGENATED CASTOR OIL,METHYLPROPANEDIOL,PEG/PPG-20/15 DIMETHICONE,PEG-30 DIPOLYHYDROXYSTEARATE,DIMETHICONE/VINYL DIMETHICONE CROSSPOLYMER Soft (POLYSILICONE-11),PROPANEDIOL,SILICON DIOXIDE (SILICA),SODIUM CHLORIDE, .ALPHA.-TOCOPHEROL ACETATE (TOCOPHERYL ACETATE),TRIETHOXYCAPRYLYLSILANE, WATER

Description

PERFORMANCE+
BROAD SPECTRUM SPF 42 SUNSCREEN FOR SPORT
NON-GREASY
CLEAR ZINC OXIDE
WATER RESISTANT (80 MIN)
FRAGRANCE + PARABEN FREE